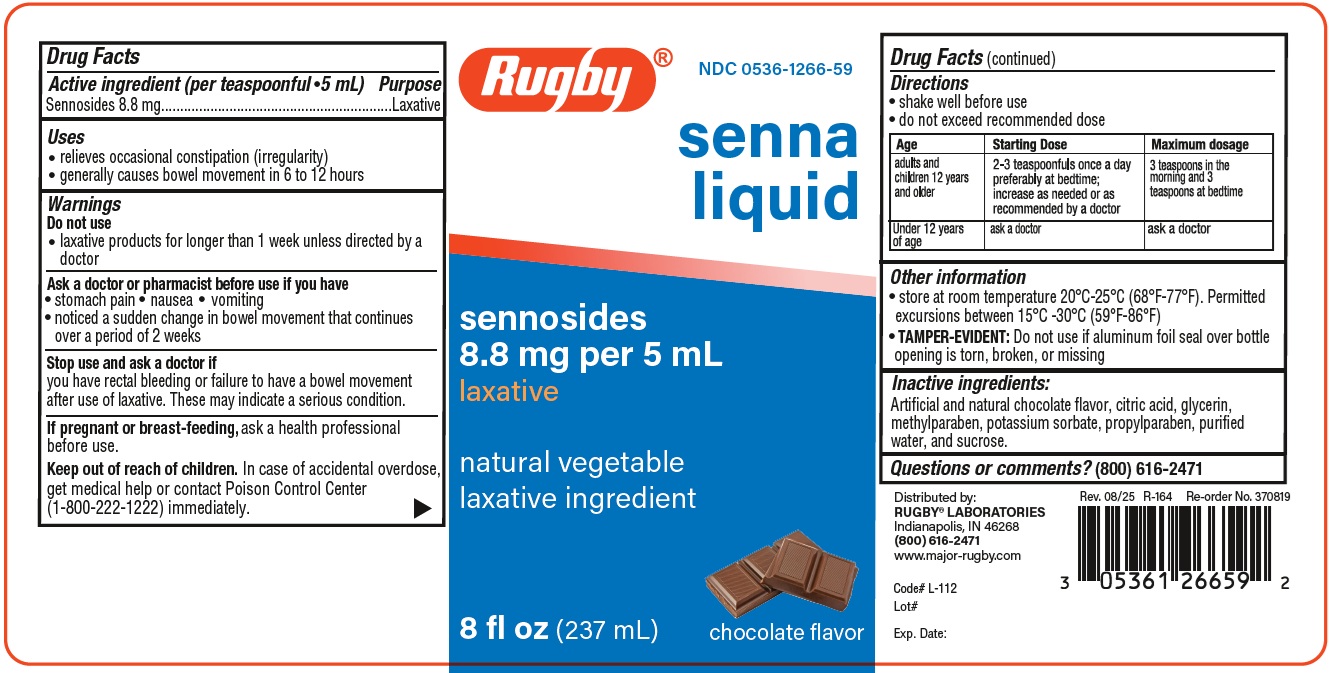 DRUG LABEL: Senna Liquid
NDC: 0536-1266 | Form: LIQUID
Manufacturer: RUGBY LABORATORIES
Category: otc | Type: HUMAN OTC DRUG LABEL
Date: 20251230

ACTIVE INGREDIENTS: SENNOSIDES 8.8 mg/5 mL
INACTIVE INGREDIENTS: METHYLPARABEN; PROPYLENE GLYCOL; PROPYLPARABEN; WATER; SUCROSE

Rugby- Senna 1266

ACTIVE INGREDIENT

Per teaspoonful-5mL

Sennosides - 8.8 mg

Purpose

Laxative

Uses

- relieves occasional constipation (irregularity)
- generally causes bowel movment in 6 to 12 hours

Warnings

Do not use

- laxative products for longer than 1 week unless directed by a doctor

Ask a doctor or pharmacis before use if you have

- stomach pain
- nausea
- vomiting
- noticed a sudden changed in bowel movement that continues over a period of 2 weeks

Stope use and ask a doctor if

you have rectal bleeding or failure to have a bowel movemebt after use of laxative. They may indicate a serious condition.

PREGNANCY

If pregnant or breast-feeding ask a health professional before use

Keep out of reach of children. In case of accidental overdose, get medical help or contact a Poison Control Center (1-800-222-1222) immediately

DOSAGE AND ADMINISTRATION

- shake well before use
- Do not exceed recommended dose

Age | Starting Dose | Maximum dosage
Adults and children 12 years and older | 2-3 teaspoonfuls once a day preferably at bedtime; increase as needed or as recommended by a doctor | 3 teaspoons in the morning and 3 teaspoons at bedtime
Under 12 years of age | ask a doctor | ask a doctor

INACTIVE INGREDIENT

Inactive ingredients artificial and natural chocolate flavor, methylparaben, propylene glycol, propylparaben, purified water, and sucrose.

Questions or comments? 1-866-645-2158